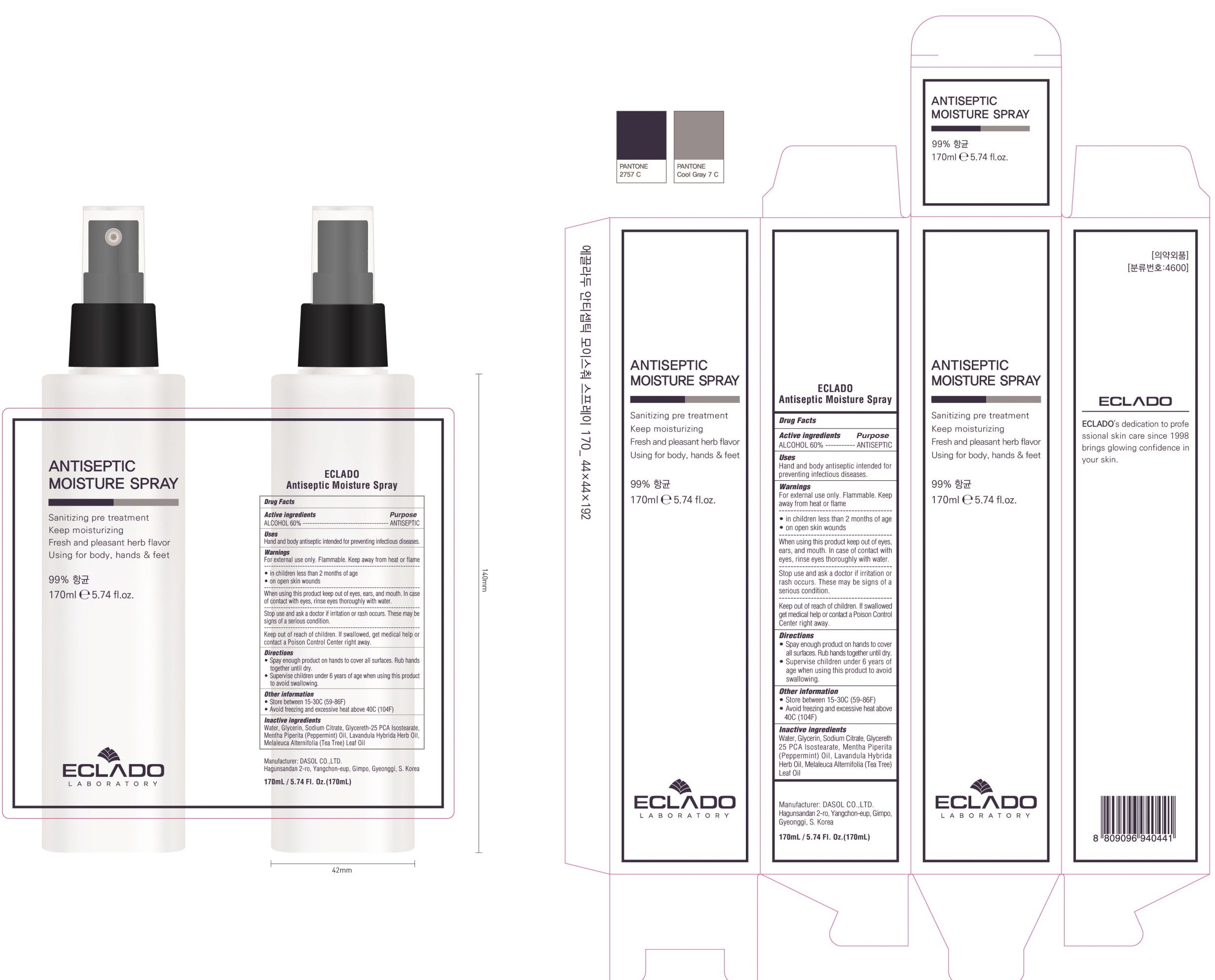 DRUG LABEL: ECLADO Antiseptic Moisture
NDC: 76900-010 | Form: SPRAY
Manufacturer: Laon Cosmetic
Category: otc | Type: HUMAN OTC DRUG LABEL
Date: 20200506

ACTIVE INGREDIENTS: ALCOHOL 102 mL/170 mL
INACTIVE INGREDIENTS: Water; Glycerin; Sodium Citrate; PEPPERMINT OIL; TEA TREE OIL

ACTIVE INGREDIENT

Active ingredients: 60%

INACTIVE INGREDIENT

Inactive ingredients:

Water, Glycerin, Sodium Citrate, Glycereth-25 PCA Isostearate, Mentha Piperita (Peppermint) Oil, Lavandula Hybrida Herb Oil, Melaleuca Alternifolia (Tea Tree) Leaf Oil

PURPOSE

Purpose: ANTISEPTIC

WARNINGS

For external use only. Flammable. Keep away from heat or flame
--------------------------------------------------------------------------------------------------------
Do not use
• in children less than 2 months of age
• on open skin wounds
--------------------------------------------------------------------------------------------------------
When using this product keep out of eyes, ears, and mouth. In case of contact with eyes, rinse eyes thoroughly with water.
--------------------------------------------------------------------------------------------------------
Stop use and ask a doctor if irritation or rash occurs. These may be signs of a serious condition.

Keep out of reach of children. If swallowed, get medical help or contact a Poison Control Center right away.

Uses

Hand and body antiseptic intended for preventing infectious diseases.

Directions

• Spay enough product on hands to cover all surfaces. Rub hands together until dry.
• Supervise children under 6 years of age when using this product to avoid swallowing.

Other Information

• Store between 15-30C (59-86F)
• Avoid freezing and excessive heat above 40C (104F)